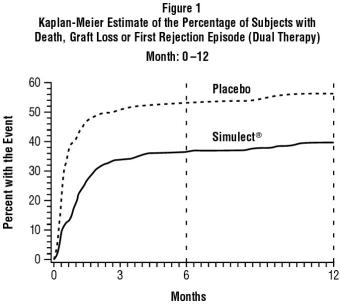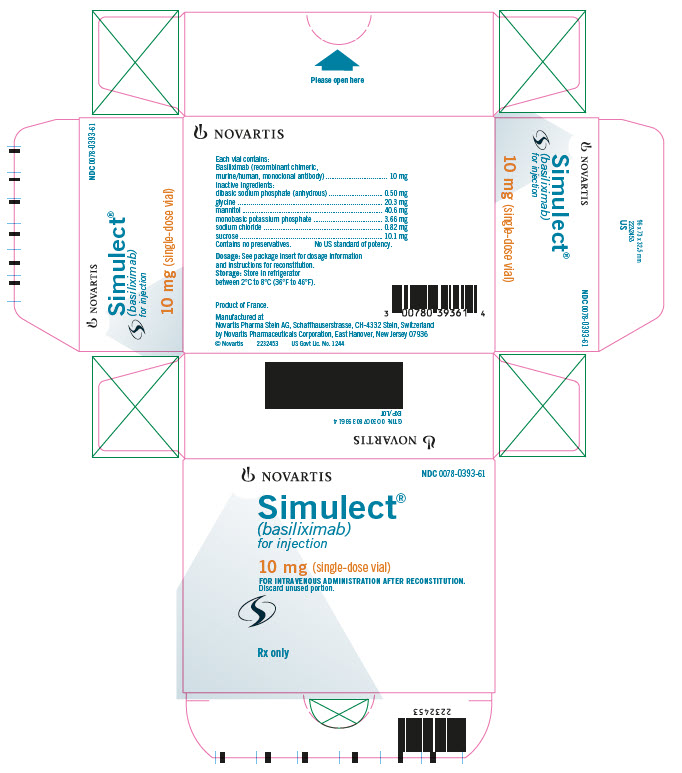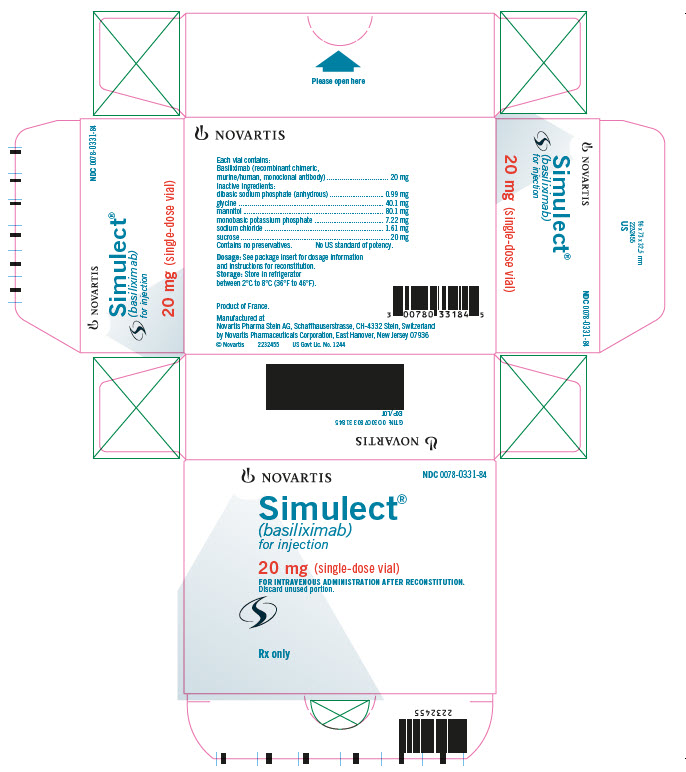 DRUG LABEL: Simulect
NDC: 0078-0393 | Form: INJECTION, POWDER, FOR SOLUTION
Manufacturer: Novartis Pharmaceuticals Corporation
Category: prescription | Type: HUMAN PRESCRIPTION DRUG LABEL
Date: 20251212

ACTIVE INGREDIENTS: BASILIXIMAB 10 mg/2.5 mL
INACTIVE INGREDIENTS: SODIUM PHOSPHATE, DIBASIC, ANHYDROUS 0.50 mg/2.5 mL; GLYCINE 20 mg/2.5 mL; MANNITOL 41 mg/2.5 mL; POTASSIUM PHOSPHATE, MONOBASIC 3.66 mg/2.5 mL; SODIUM CHLORIDE 0.82 mg/2.5 mL; SUCROSE 10 mg/2.5 mL

Simulect®
(basiliximab)
For Injection
Rx only
Prescribing Information

WARNING

Only physicians experienced in immunosuppression therapy and management of organ transplantation patients should prescribe Simulect® (basiliximab). The physician responsible for Simulect administration should have complete information requisite for the follow-up of the patient. Patients receiving the drug should be managed in facilities equipped and staffed with adequate laboratory and supportive medical resources.

DESCRIPTION

Basiliximab is a chimeric (murine/human) monoclonal antibody (IgG1к), produced by recombinant DNA technology, that functions as an immunosuppressive agent, specifically binding to and blocking the interleukin-2 receptor α-chain (IL-2Rα, also known as CD25 antigen) on the surface of activated T-lymphocytes. Based on the amino acid sequence, the calculated molecular weight of the protein is 144 kilodaltons. It is a glycoprotein obtained from fermentation of an established mouse myeloma cell line genetically engineered to express plasmids containing the human heavy and light chain constant region genes and mouse heavy and light chain variable region genes encoding the RFT5 antibody that binds selectively to the IL-2Rα.

Simulect® (basiliximab) for injection is a sterile, preservative-free lyophilisate, which is available in single-dose vials and is available in 10 mg and 20 mg strengths for intravenous administration after reconstitution.

Each 10-mg vial contains 10 mg of basiliximab, and dibasic sodium phosphate (anhydrous) (0.50 mg), glycine (20.3 mg), mannitol (40.6 mg), monobasic potassium phosphate (3.66 mg), sodium chloride (0.82 mg), and sucrose (10.1 mg) to be reconstituted in 2.5 mL of Sterile Water for Injection, USP.

Each 20-mg vial contains 20 mg of basiliximab, and dibasic sodium phosphate (anhydrous) (0.99 mg), glycine (40.1 mg), mannitol (80.1 mg), monobasic potassium phosphate (7.22 mg), sodium chloride (1.61 mg), and sucrose (20 mg) to be reconstituted in 5 mL of Sterile Water for Injection, USP.

CLINICAL PHARMACOLOGY

General

Mechanism of Action: Basiliximab functions as an IL-2 receptor antagonist by binding with high affinity (Ka = 1 x 10^10 M^-1) to the alpha chain of the high affinity IL-2 receptor complex and inhibiting IL-2 binding. Basiliximab is specifically targeted against IL-2Rα, which is selectively expressed on the surface of activated T-lymphocytes. This specific high affinity binding of Simulect® (basiliximab) to IL-2Rα competitively inhibits IL-2-mediated activation of lymphocytes, a critical pathway in the cellular immune response involved in allograft rejection.

While in the circulation, Simulect impairs the response of the immune system to antigenic challenges. Whether the ability to respond to repeated or ongoing challenges with those antigens returns to normal after Simulect is cleared is unknown (see PRECAUTIONS).

Pharmacokinetics

Adults: Single-dose and multiple-dose pharmacokinetic studies have been conducted in patients undergoing first kidney transplantation. Cumulative doses ranged from 15 mg up to 150 mg. Peak mean ± SD serum concentration following intravenous infusion of 20 mg over 30 minutes is 7.1 ± 5.1 mg/L. There is a dose-proportional increase in Cmax and area under the curve (AUC) up to the highest tested single dose of 60 mg. The volume of distribution at steady state is 8.6 ± 4.1 L. The extent and degree of distribution to various body compartments have not been fully studied. The terminal half-life is 7.2 ± 3.2 days. Total body clearance is 41 ± 19 mL/h. No clinically relevant influence of body weight or gender on distribution volume or clearance has been observed in adult patients. Elimination half-life was not influenced by age (20-69 years), gender or race (see DOSAGE AND ADMINISTRATION).

Pediatric: The pharmacokinetics of Simulect have been assessed in 39 pediatric patients undergoing renal transplantation. In infants and children (1-11 years of age, n = 25), the distribution volume and clearance were reduced by about 50% compared to adult renal transplantation patients. The volume of distribution at steady state was 4.8 ± 2.1 L, half-life was 9.5 ± 4.5 days and clearance was 17 ± 6 mL/h. Disposition parameters were not influenced to a clinically relevant extent by age (1-11 years of age), body weight (9-37 kg) or body surface area (0.44-1.20 m^2) in this age group. In adolescents (12-16 years of age, n = 14), disposition was similar to that in adult renal transplantation patients. The volume of distribution at steady state was 7.8 ± 5.1 L, half-life was 9.1 ± 3.9 days and clearance was 31 ± 19 mL/h (see DOSAGE AND ADMINISTRATION).

Pharmacodynamics

Complete and consistent binding to IL-2Rα in adults is maintained as long as serum Simulect levels exceed 0.2 mcg/mL. As concentrations fall below this threshold, the IL-2Rα sites are no longer fully bound and the number of T-cells expressing unbound IL-2Rα returns to pretherapy values within 1-2 weeks. The relationship between serum concentration and receptor saturation was assessed in 13 pediatric patients and was similar to that characterized in adult renal transplantation patients. In vitro studies using human tissues indicate that Simulect binds only to lymphocytes.

The duration of clinically relevant IL-2 receptor blockade after the recommended course of Simulect is not known. When basiliximab was added to a regimen of cyclosporine, USP (MODIFIED) and corticosteroids in adult patients, the duration of IL-2Rα saturation was 36 ± 14 days (mean ± SD), similar to that observed in pediatric patients (36 ± 14 days) (see DOSAGE AND ADMINISTRATION). When basiliximab was added to a triple therapy regimen consisting of cyclosporine, USP (MODIFIED), corticosteroids, and azathioprine in adults, the duration was 50 ± 20 days and when added to cyclosporine, USP (MODIFIED), corticosteroids, and mycophenolate mofetil in adults, the duration was 59 ± 17 days (see PRECAUTIONS, Drug Interactions). No significant changes to circulating lymphocyte numbers or cell phenotypes were observed by flow cytometry.

CLINICAL STUDIES

The safety and efficacy of Simulect® (basiliximab) for the prophylaxis of acute organ rejection in adults following cadaveric- or living-donor renal transplantation were assessed in four randomized, double-blind, placebo-controlled clinical studies (1,184 patients). Of these four, two studies (Study 1 [EU/CAN] and Study 2 [US Study]) compared two 20-mg doses of Simulect with placebo, each administered intravenously as an infusion, as part of a standard immunosuppressive regimen comprised of cyclosporine, USP (MODIFIED) and corticosteroids. The other two controlled studies compared two 20-mg doses of Simulect with placebo, each administered intravenously as a bolus injection, as part of a standard triple-immunosuppressive regimen comprised of cyclosporine, USP (MODIFIED), corticosteroids and either azathioprine or mycophenolate mofetil (Study 3 and Study 4, respectively). The first dose of Simulect or placebo was administered within 2 hours prior to transplantation surgery (Day 0) and the second dose administered on Day 4 post-transplantation. The regimen of Simulect was chosen to provide 30-45 days of IL-2Rα saturation.

Seven hundred twenty-nine patients were enrolled in the two studies using a dual maintenance immunosuppressive regimen comprised of cyclosporine, USP (MODIFIED) and corticosteroids, of which 363 patients were treated with Simulect and 358 patients were placebo-treated. Study 1 was conducted at 21 sites in Europe and Canada (EU/CAN Study); Study 2 was conducted at 21 sites in the USA (US Study). Patients 18-75 years of age undergoing first cadaveric- (Study 1 and Study 2) or living-donor (Study 2 only) renal transplantation, with ≥ 1 HLA mismatch, were enrolled.^1,2

The primary efficacy endpoint in both studies was the incidence of death, graft loss or an episode of acute rejection during the first 6 months post-transplantation. Secondary efficacy endpoints included the primary efficacy variable measured during the first 12 months post-transplantation, the incidence of biopsy-confirmed acute rejection during the first 6 and 12 months post-transplantation and patient survival and graft survival, each measured at 12 months post-transplantation. Table 1 summarizes the results of these studies. Figure 1 displays the Kaplan-Meier estimates of the percentage of patients by treatment group experiencing the primary efficacy endpoint during the first 12 months post-transplantation for Study 2. Patients in both studies receiving Simulect experienced a significantly lower incidence of biopsy-confirmed rejection episodes at both 6 and 12 months post-transplantation. There was no difference in the rate of delayed graft function, patient survival, or graft survival between Simulect-treated patients and placebo-treated patients in either study.

There was no evidence that the clinical benefit of Simulect was limited to specific subpopulations based on age, gender, race, donor type (cadaveric or living donor allograft), or history of diabetes mellitus.

Table 1. Efficacy Parameters (Percentage of Patients)
Dual-therapy Regimen (cyclosporine* and corticosteroids)
 | Study 1 |  |  | Study 2
 | Placebo (N = 185) | Simulect® (N = 190) | p-value | Placebo (N = 173) | Simulect® (N = 173) | p-value
Primary endpoint
Death, graft loss or acute rejection episode (0-6 months)
 | 57% | 42% | 0.003 | 55% | 38% | 0.002
Secondary endpoints
Death, graft loss or acute rejection episode (0-12 months)
 | 60% | 46% | 0.007 | 58% | 41% | 0.001
Biopsy-confirmed rejection episode (0-6 months)
 | 44% | 30% | 0.007 | 46% | 33% | 0.015
Biopsy-confirmed rejection episode (0-12 months)
 | 46% | 32% | 0.005 | 49% | 35% | 0.009
Patient survival (12 months)
 | 97% | 95% | 0.29 | 96% | 97% | 0.56
Patients with functioning graft (12 months)
 | 87% | 88% | 0.70 | 93% | 95% | 0.50
*USP (MODIFIED).

Two double-blind, randomized, placebo-controlled studies (Study 3 and Study 4) assessed the safety and efficacy of Simulect for the prophylaxis of acute renal transplant rejection in adults when used in combination with a triple immunosuppressive regimen. In Study 3, 340 patients were concomitantly treated with cyclosporine, USP (MODIFIED), corticosteroids and azathioprine (AZA), of which 168 patients were treated with Simulect and 172 patients were treated with placebo. In Study 4, 123 patients were concomitantly treated with cyclosporine, USP (MODIFIED), corticosteroids and mycophenolate mofetil (MMF), of which 59 patients were treated with Simulect and 64 patients were treated with placebo. Patients 18-70 years of age undergoing first or second cadaveric or living donor (related or unrelated) renal transplantation were enrolled in both studies.

The results of Study 3 are shown in Table 2. These results are consistent with the findings from Study 1 and Study 2.

Table 2. Efficacy Parameters (Percentage of Patients)
Study 3: Triple-therapy Regimen (cyclosporine*, corticosteroids, and azathioprine)
 | Placebo | Simulect®
 | (N = 172) | (N = 168) | p-value
Primary endpoint
Acute rejection episode (0-6 months) | 35% | 21% | 0.005
Secondary endpoints
Death, graft loss or acute rejection episode (0-6 months) | 40% | 26% | 0.008
Biopsy-confirmed rejection episode (0-6 months) | 29% | 18% | 0.023
Patient survival (12 months) | 97% | 98% | 1.000
Patients with functioning graft (12 months) | 88% | 90% | 0.599
*USP (MODIFIED).

In Study 4, the percentage of patients experiencing biopsy-proven acute rejection by 6 months was 15% (9 of 59 patients) in the Simulect group and 27% (17 of 64 patients) in the placebo group. Although numerically lower, the difference in acute rejection was not significant.

In a multicenter, randomized, double-blind, placebo-controlled trial of Simulect for the prevention of allograft rejection in liver transplant recipients (n = 381) receiving concomitant cyclosporine, USP (MODIFIED) and steroids, the incidence of the combined endpoint of death, graft loss, or first biopsy-confirmed rejection episode at either 6 or 12 months was similar between patients randomized to receive Simulect and those randomized to receive placebo.

The efficacy of Simulect for the prophylaxis of acute rejection in recipients of a second renal allograft has not been demonstrated.

Long-Term Followup

Five-year patient survival and graft survival data were provided by 71% and 58% of the original subjects of Study 1 and Study 2, respectively. Subjects in both studies continued to receive a dual-therapy regimen with cyclosporine, USP (MODIFIED) and corticosteroid. No difference was observed between groups in the 5-year graft survival in either Study 1 (91% Simulect group, 92% placebo group) or Study 2 (85% Simulect group, 86% placebo group). In Study 1, patient survival was lower in the Simulect-treated patients compared to the placebo-treated patients (142/163 [87%] vs. 156/164 [95%], respectively). The cause of this difference in survival is unknown. The data do not indicate an increase in malignancy- or infection-related mortality. In Study 2, patient survival in the placebo group (90%) was the same compared to Simulect group (90%).

INDICATIONS AND USAGE

Simulect® (basiliximab) is indicated for the prophylaxis of acute organ rejection in patients receiving renal transplantation when used as part of an immunosuppressive regimen that includes cyclosporine, USP (MODIFIED), and corticosteroids.

The efficacy of Simulect for the prophylaxis of acute rejection in recipients of other solid organ allografts has not been demonstrated.

CONTRAINDICATIONS

Simulect® (basiliximab) is contraindicated in patients with known hypersensitivity to basiliximab or any other component of the formulation. See composition of Simulect under DESCRIPTION.

General

Simulect® (basiliximab) should be administered under qualified medical supervision. Patients should be informed of the potential benefits of therapy and the risks associated with administration of immunosuppressive therapy.

While neither the incidence of lymphoproliferative disorders nor opportunistic infections was higher in Simulect-treated patients than in placebo-treated patients, patients on immunosuppressive therapy are at increased risk for developing these complications and should be monitored accordingly.

Hypersensitivity

Severe acute (onset within 24 hours) hypersensitivity reactions, including anaphylaxis have been observed both on initial exposure to Simulect and/or following re-exposure after several months. These reactions may include hypotension, tachycardia, cardiac failure, dyspnea, wheezing, bronchospasm, pulmonary edema, respiratory failure, urticaria, rash, pruritus, and/or sneezing. Extreme caution should be exercised in all patients previously given Simulect when being administered a subsequent course of Simulect. A subgroup of patients may be particularly at risk of developing severe hypersensitivity reactions on re-administration. These are patients in whom concomitant immunosuppression was discontinued prematurely (e.g., due to abandoned transplantation or early loss of the graft) following the initial administration of Simulect. If a severe hypersensitivity reaction occurs, therapy with Simulect should be permanently discontinued. Medications for the treatment of severe hypersensitivity reactions, including anaphylaxis should be available for immediate use.

PRECAUTIONS

General

It is not known whether Simulect® (basiliximab) use will have a long-term effect on the ability of the immune system to respond to antigens first encountered during Simulect-induced immunosuppression.

Immunogenicity

Of renal transplantation patients treated with Simulect and tested for anti-idiotype antibodies, 4/339 developed an anti-idiotype antibody response, with no deleterious clinical effect upon the patient. In none of these cases was there evidence that the presence of anti-idiotype antibody accelerated Simulect clearance or decreased the period of receptor saturation. In Study 2, the incidence of human anti-murine antibody (HAMA) in renal transplantation patients treated with Simulect was 2/138 in patients not exposed to muromonab-CD3 and 4/34 in patients who subsequently received muromonab-CD3. The available clinical data on the use of muromonab-CD3 in patients previously treated with Simulect suggest that subsequent use of muromonab-CD3 or other murine anti-lymphocytic antibody preparations is not precluded.

These data reflect the percentage of patients whose test results were considered positive for antibodies to Simulect in an ELISA assay, and are highly dependent on the sensitivity and specificity of the assay. Additionally the observed incidence of antibody positivity in an assay may be influenced by several factors, including sample handling, concomitant medications, and underlying disease. For these reasons, comparison of the incidence of antibodies to Simulect with the incidence of antibodies to other products may be misleading.

Drug Interactions

No dose adjustment is necessary when Simulect is added to triple-immunosuppression regimens, including cyclosporine, corticosteroids, and either azathioprine or mycophenolate mofetil. Three clinical trials have investigated Simulect use in combination with triple-therapy regimens. Pharmacokinetics were assessed in two of these trials. Total body clearance of Simulect was reduced by an average 22% and 51% when azathioprine and mycophenolate mofetil, respectively, were added to a regimen consisting of cyclosporine, USP (MODIFIED) and corticosteroids. Nonetheless, the range of individual Simulect clearance values in the presence of azathioprine (12-57 mL/h) or mycophenolate mofetil (7-54 mL/h) did not extend outside the range observed with dual therapy (10-78 mL/h). The following medications have been administered in clinical trials with Simulect with no increase in adverse reactions: ATG/ALG, azathioprine, corticosteroids, cyclosporine, mycophenolate mofetil, and muromonab-CD3.

Carcinogenesis/Mutagenesis/Impairment of Fertility

No mutagenic potential of Simulect was observed in the in vitro assays with Salmonella (Ames) and V79 Chinese hamster cells. No long-term or fertility studies in laboratory animals have been performed to evaluate the potential of Simulect to produce carcinogenicity or fertility impairment, respectively.

There are no adequate and well-controlled studies in pregnant women. No maternal toxicity, embryotoxicity, or teratogenicity was observed in cynomolgus monkeys 100 days post coitum following dosing with basiliximab during the organogenesis period; blood levels in pregnant monkeys were 13-fold higher than those seen in human patients. Immunotoxicology studies have not been performed in the offspring. Because IgG molecules are known to cross the placental barrier, because the IL-2 receptor may play an important role in development of the immune system, and because animal reproduction studies are not always predictive of human response, Simulect should only be used in pregnant women when the potential benefit justifies the potential risk to the fetus. Women of childbearing potential should use effective contraception before beginning Simulect therapy, during therapy, and for 4 months after completion of Simulect therapy.

Nursing Mothers

It is not known whether Simulect is excreted in human milk. Because many drugs, including human antibodies are excreted in human milk, and because of the potential for adverse reactions, a decision should be made to discontinue nursing or to discontinue the drug, taking into account the importance of the drug to the mother.

Pediatric Use

No randomized, placebo-controlled studies have been completed in pediatric patients. In a safety and pharmacokinetic study, 41 pediatric patients (1-11 years of age [n = 27], 12-16 years of age [n = 14], median age 8.1 years) were treated with Simulect via intravenous bolus injection in addition to standard immunosuppressive agents, including cyclosporine, USP (MODIFIED), corticosteroids, azathioprine, and mycophenolate mofetil. The acute rejection rate at 6 months was comparable to that in adults in the triple-therapy trials. The most frequently reported adverse events were hypertension, hypertrichosis, and rhinitis (49% each), urinary tract infections (46%), and fever (39%). Overall, the adverse event profile was consistent with general clinical experience in the pediatric renal transplantation population and with the profile in the controlled adult renal transplantation studies. The available pharmacokinetic data in children and adolescents are described in CLINICAL PHARMACOLOGY and DOSAGE AND ADMINISTRATION.

It is not known whether the immune response to vaccines, infection, and other antigenic stimuli administered or encountered during Simulect therapy is impaired or whether such response will remain impaired after Simulect therapy.

Geriatric Use

Controlled clinical studies of Simulect have included a small number of patients 65 years and older (Simulect 28; placebo 32). From the available data comparing Simulect and placebo-treated patients, the adverse event profile in patients ≥ 65 years of age is not different from patients < 65 years of age and no age-related dosing adjustment is required. Caution must be used in giving immunosuppressive drugs to elderly patients.

ADVERSE REACTIONS

Because clinical trials are conducted under widely varying conditions, adverse reaction rates observed in the clinical trials of a drug cannot be directly compared to rates in the clinical trials of another drug and may not reflect the rates observed in practice. The adverse reaction information from clinical trials does, however, provide a basis for identifying the adverse events that appear to be related to drug use and for approximating rates.

The incidence of adverse events for Simulect® (basiliximab) was determined in four randomized, double-blind, placebo-controlled clinical trials for the prevention of renal allograft rejection. Two of the studies (Study 1 and Study 2), used a dual maintenance immunosuppressive regimen comprised of cyclosporine, USP (MODIFIED) and corticosteroids, whereas the other two studies (Study 3 and Study 4) used a triple-immunosuppressive regimen comprised of cyclosporine, USP (MODIFIED), corticosteroids, and either azathioprine or mycophenolate mofetil.

Simulect did not appear to add to the background of adverse events seen in organ transplantation patients as a consequence of their underlying disease and the concurrent administration of immunosuppressants and other medications. Adverse events were reported by 96% of the patients in the placebo-treated group and 96% of the patients in the Simulect-treated group. In the four placebo-controlled studies, the pattern of adverse events in 590 patients treated with the recommended dose of Simulect was similar to that in 594 patients treated with placebo. Simulect did not increase the incidence of serious adverse events observed compared with placebo.

The most frequently reported adverse events were gastrointestinal disorders, reported in 69% of Simulect-treated patients and 67% of placebo-treated patients.

The incidence and types of adverse events were similar in Simulect-treated and placebo-treated patients. The following adverse events occurred in ≥ 10% of Simulect-treated patients: Gastrointestinal System: constipation, nausea, abdominal pain, vomiting, diarrhea, dyspepsia; Body as a Whole-General: pain, peripheral edema, fever, viral infection; Metabolic and Nutritional: hyperkalemia, hypokalemia, hyperglycemia, hypercholesterolemia, hypophosphatemia, hyperuricemia; Urinary System: urinary tract infection; Respiratory System: dyspnea, upper respiratory tract infection; Skin and Appendages: surgical wound complications, acne; Cardiovascular Disorders-General: hypertension; Central and Peripheral Nervous System: headache, tremor; Psychiatric: insomnia; Red Blood Cell: anemia.

The following adverse events, not mentioned above, were reported with an incidence of ≥ 3% and < 10% in pooled analysis of patients treated with Simulect in the four controlled clinical trials, or in an analysis of the two dual-therapy trials: Body as a Whole-General: accidental trauma, asthenia, chest pain, increased drug level, infection, face edema, fatigue, dependent edema, generalized edema, leg edema, malaise, rigors, sepsis; Cardiovascular: abnormal heart sounds, aggravated hypertension, angina pectoris, cardiac failure, chest pain, hypotension; Endocrine: increased glucocorticoids; Gastrointestinal: enlarged abdomen, esophagitis, flatulence, gastrointestinal disorder, gastroenteritis, GI hemorrhage, gum hyperplasia, melena, moniliasis, ulcerative stomatitis; Heart Rate and Rhythm: arrhythmia, atrial fibrillation, tachycardia; Metabolic and Nutritional: acidosis, dehydration, diabetes mellitus, fluid overload, hypercalcemia, hyperlipemia, hypertriglyceridemia, hypocalcemia, hypoglycemia, hypomagnesemia, hypoproteinemia, weight increase; Musculoskeletal: arthralgia, arthropathy, back pain, bone fracture, cramps, hernia, myalgia, leg pain; Nervous System: dizziness, neuropathy, paraesthesia, hypoesthesia; Platelet and Bleeding: hematoma, hemorrhage, purpura, thrombocytopenia, thrombosis; Psychiatric: agitation, anxiety, depression; Red Blood Cell: polycythemia; Reproductive Disorders, Male: genital edema, impotence; Respiratory: bronchitis, bronchospasm, abnormal chest sounds, coughing, pharyngitis, pneumonia, pulmonary disorder, pulmonary edema, rhinitis, sinusitis; Skin and Appendages: cyst, herpes simplex, herpes zoster, hypertrichosis, pruritus, rash, skin disorder, skin ulceration; Urinary: albuminuria, bladder disorder, dysuria, frequent micturition, hematuria, increased non-protein nitrogen, oliguria, abnormal renal function, renal tubular necrosis, surgery, ureteral disorder, urinary retention; Vascular Disorders: vascular disorder; Vision Disorders: cataract, conjunctivitis, abnormal vision; White Blood Cell: leucopenia. Among these events, leucopenia and hypertriglyceridemia occurred more frequently in the two triple-therapy studies using azathioprine and mycophenolate mofetil than in the dual-therapy studies.

Malignancies

The incidence of malignancies in the controlled clinical trials of renal transplant was not significantly different between groups at 1 year (9/590 Simulect-treated patients vs. 12/594 placebo-treated patients) or among patients with 5-year follow-up from Studies 1 and 2 (21/295 Simulect-treated patients vs. 21/291 placebo-treated patients). The incidence of lymphoproliferative disease was not significantly different between groups, and less than 1% in the Simulect-treated patients.

Infections

The overall incidence of cytomegalovirus infection was similar in Simulect- and placebo-treated patients (15% vs. 17%) receiving a dual- or triple-immunosuppression regimen. However, in patients receiving a triple-immunosuppression regimen, the incidence of serious cytomegalovirus infection was higher in Simulect-treated patients compared to placebo-treated patients (11% vs. 5%). The rates of infections, serious infections, and infectious organisms were similar in the Simulect- and placebo-treatment groups among dual- and triple-therapy treated patients.

Postmarketing Experience

Severe acute hypersensitivity reactions, including anaphylaxis characterized by hypotension, tachycardia, cardiac failure, dyspnea, wheezing, bronchospasm, pulmonary edema, respiratory failure, urticaria, rash, pruritus, and/or sneezing, as well as capillary leak syndrome and cytokine release syndrome, have been reported during post-marketing experience with Simulect.

OVERDOSAGE

A maximum tolerated dose of Simulect® (basiliximab) has not been determined in patients. During the course of clinical studies, Simulect has been administered to adult renal transplantation patients in single doses of up to 60 mg, or in divided doses over 3-5 days of up to 120 mg, without any associated serious adverse events. There has been one spontaneous report of a pediatric renal transplantation patient who received a single 20-mg dose (2.3 mg/kg) without adverse events.

DOSAGE AND ADMINISTRATION

Simulect® (basiliximab) is used as part of an immunosuppressive regimen that includes cyclosporine, USP (MODIFIED) and corticosteroids. Simulect is for central or peripheral intravenous administration only. Reconstituted Simulect should be given either as a bolus injection or diluted to a volume of 25 mL (10-mg vial) or 50 mL (20-mg vial) with 0.9% Sodium Chloride Injection, USP or 5% Dextrose Injection, USP and administered as an intravenous infusion over 20 to 30 minutes. Bolus administration may be associated with nausea, vomiting and local reactions, including pain.

Simulect should only be administered once it has been determined that the patient will receive the graft and concomitant immunosuppression. Patients previously administered Simulect should only be re-exposed to a subsequent course of therapy with extreme caution due to the potential risk of hypersensitivity (see WARNINGS).

Parenteral drug products should be inspected visually for particulate matter and discoloration before administration. After reconstitution, Simulect should be a clear-to-opalescent, colorless solution. If particulate matter is present or the solution is colored, do not use.

Care must be taken to assure sterility of the prepared solution because the drug product does not contain any antimicrobial preservatives or bacteriostatic agents.

It is recommended that after reconstitution, the solution should be used immediately. If not used immediately, it can be stored at 2ºC to 8ºC (36ºF to 46ºF) for 24 hours or at room temperature for 4 hours. Discard the reconstituted solution if not used within 24 hours.

No incompatibility between Simulect and polyvinyl chloride bags or infusion sets has been observed. No data are available on the compatibility of Simulect with other intravenous substances. Other drug substances should not be added or infused simultaneously through the same intravenous line.

Adults

In adult patients, the recommended regimen is two doses of 20 mg each. The first 20-mg dose should be given within 2 hours prior to transplantation surgery. The recommended second 20-mg dose should be given 4 days after transplantation. The second dose should be withheld if complications, such as severe hypersensitivity reactions to Simulect or graft loss occur.

Pediatric

In pediatric patients weighing less than 35 kg, the recommended regimen is two doses of 10 mg each. In pediatric patients weighing 35 kg or more, the recommended regimen is two doses of 20 mg each. The first dose should be given within 2 hours prior to transplantation surgery. The recommended second dose should be given 4 days after transplantation. The second dose should be withheld if complications, such as severe hypersensitivity reactions to Simulect or graft loss occur.

Reconstitution of 10 mg Simulect® Vial

To prepare the reconstituted solution, add 2.5 mL of Sterile Water for Injection, USP, using aseptic technique, to the vial containing the Simulect powder. Shake the vial gently to dissolve the powder.

The reconstituted solution is isotonic and may be given either as a bolus injection or diluted to a volume of 25 mL with 0.9% Sodium Chloride Injection, USP or 5% Dextrose Injection, USP for infusion. When mixing the solution, gently invert the bag in order to avoid foaming; DO NOT SHAKE.

Reconstitution of 20 mg Simulect® Vial

To prepare the reconstituted solution, add 5 mL of Sterile Water for Injection, USP, using aseptic technique, to the vial containing the Simulect powder. Shake the vial gently to dissolve the powder.

The reconstituted solution is isotonic and may be given either as a bolus injection or diluted to a volume of 50 mL with 0.9% Sodium Chloride Injection, USP or 5% Dextrose Injection, USP for infusion. When mixing the solution, gently invert the bag in order to avoid foaming; DO NOT SHAKE.

HOW SUPPLIED

Simulect® (basiliximab) is supplied in a single-dose glass vial.

Each carton contains one of the following

1 Simulect 10 mg vial…………………………………………………….NDC 0078-0393-61

1 Simulect 20 mg vial…………………………………………………….NDC 0078-0331-84

Store lyophilized Simulect under refrigerated conditions at 2ºC to 8ºC (36ºF to 46ºF).

Do not use beyond the expiration date stamped on the vial.

REFERENCES

1. Kahan, B.D., Rajagopalan P.R. and Hall M., Transplantation, 67, 276-284 (1999).
2. Nashan, B., Moore R., Amlot P., Schmidt A.-G., Abeywickrama K. and Soulillou J.-P., Lancet 350, 1193-1198 (1997).

Manufactured by:
Novartis Pharmaceuticals Corporation
East Hanover, New Jersey 07936

US License No. 1244

© Novartis

T2020-125

Revised: August 2020

PRINCIPAL DISPLAY PANEL

NOVARTIS NDC 0078-0393-61

Simulect®
(basiliximab)
for injection

10 mg (single-dose vial)

FOR INTRAVENOUS ADMINISTRATION AFTER RECONSTITUTION.
Discard unused portion.

Rx only

PRINCIPAL DISPLAY PANEL

NOVARTIS NDC 0078-0331-84

Simulect®
(basiliximab)
for injection

20 mg (single-dose vial)

FOR INTRAVENOUS ADMINISTRATION AFTER RECONSTITUTION.
Discard unused portion.

Rx only